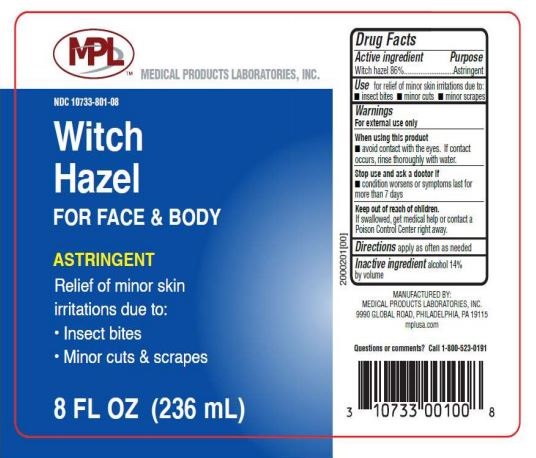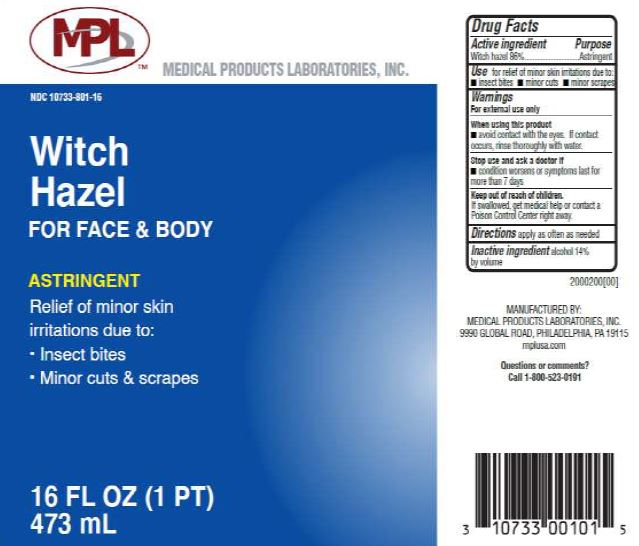 DRUG LABEL: Witch Hazel
NDC: 10733-801 | Form: LIQUID
Manufacturer: Medical Products Laboratories, Inc.
Category: otc | Type: HUMAN OTC DRUG LABEL
Date: 20241211

ACTIVE INGREDIENTS: WITCH HAZEL 86 g/100 mL
INACTIVE INGREDIENTS: ALCOHOL

Witch Hazel

Warnings

For external use only

When using this product

- avoid contact with the eyes. If contact occurs, rinse thoroughly with water.

Stop use and ask a doctor if

- condition worsens or symptoms last for more than 7 days

Keep out of reach of children.

If swallowed, get medical help or contact a Posion Control Center right away.

MANUFACTURED BY:

MEDICAL PRODUCTS LABORATORIES, INC.

9990 GLOBAL ROAD, PHILADELPHIA 19115

mplusa.com

Questions or comments? Call 1-800-523-0191

Witch Hazel For Face & Body

ASTRINGENT

Relief of minor skin irritations due to:

- Insect bites
- Minor cuts & scrapes

Active ingredient

Witch hazel 86%

Purpose

Astringent

Inactive ingredient:

alcohol 14% by volume

Use

for relief of minor skin irritations due to:

• insect bites • minor cuts • minor scrapes

Directions

apply as often as needed